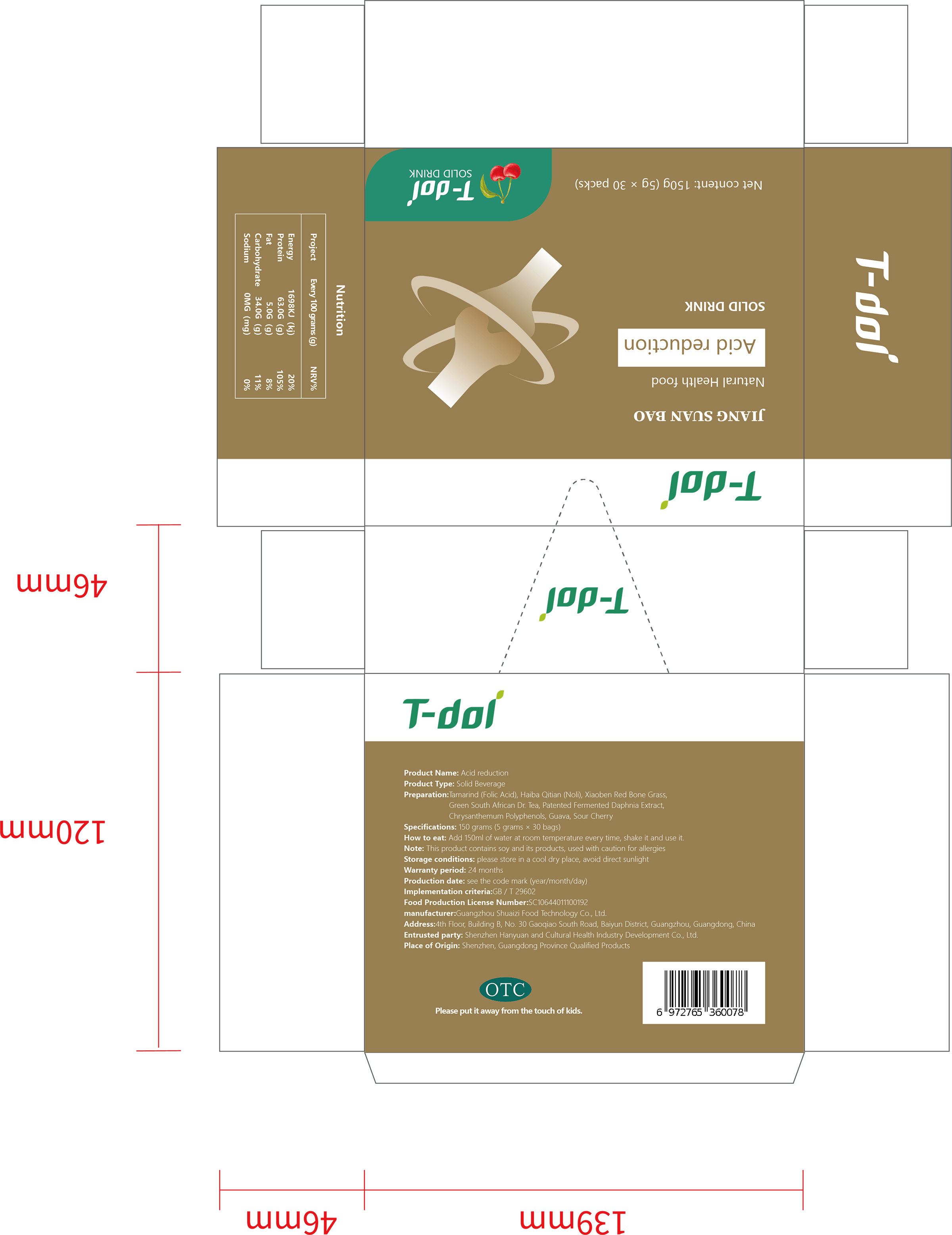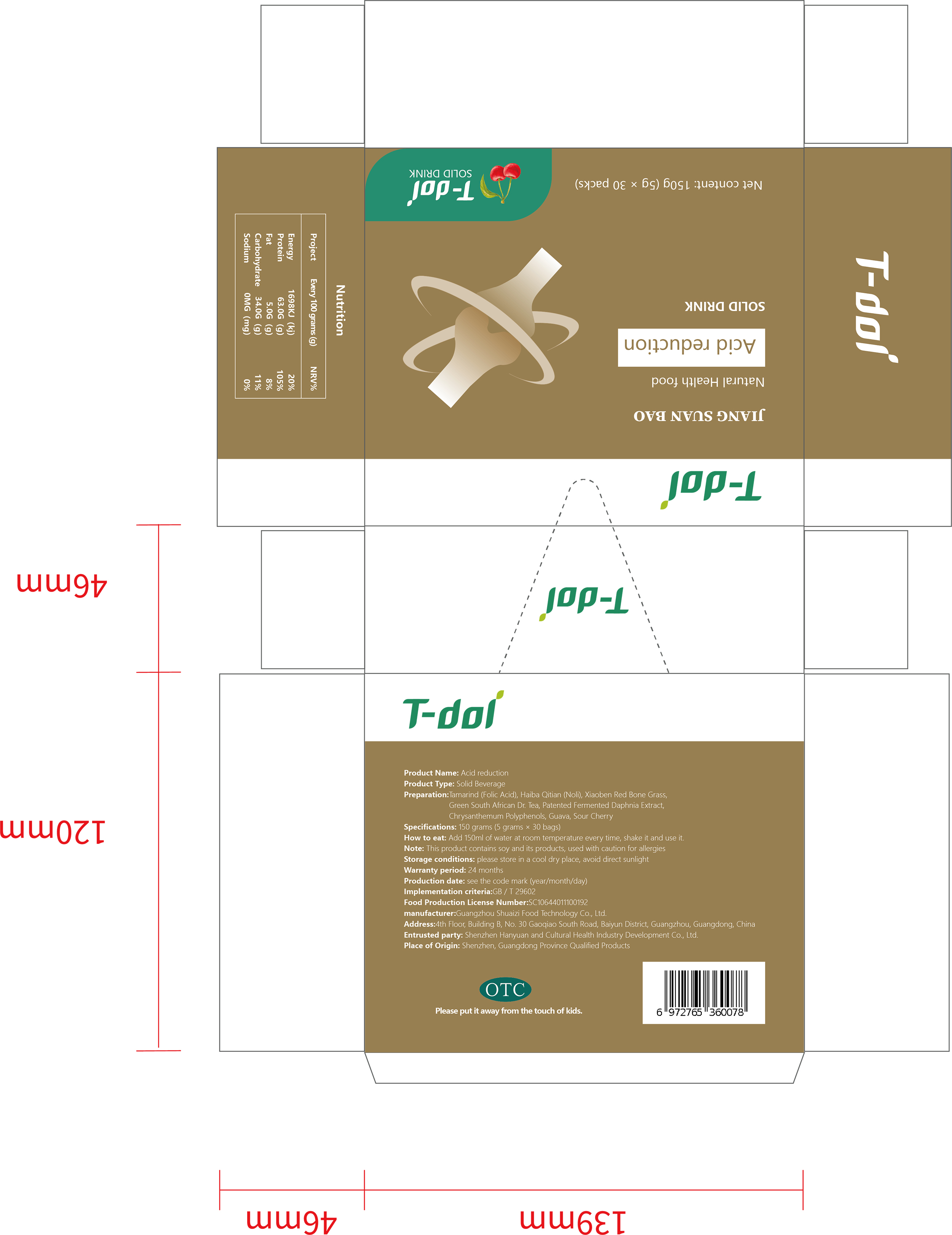 DRUG LABEL: T-dol JIANG SUAN BAO
NDC: 75018-004 | Form: POWDER
Manufacturer: Shenzhen Hanyuanhe Cultural Health Industry Development Co., Ltd.
Category: homeopathic | Type: HUMAN OTC DRUG LABEL
Date: 20191103

ACTIVE INGREDIENTS: FOLIC ACID 1.5 g/5 g
INACTIVE INGREDIENTS: SOUR CHERRY 0.1 g/5 g; NOLINIUM 1.5 g/5 g; ASPALATHUS LINEARIS WHOLE 0.1 g/5 g; GUAVA 0.1 g/5 g; PLATOSTOMA PALUSTRE WHOLE 1.5 g/5 g; BARLEY 0.1 g/5 g; CHRYSANTHEMIN 0.1 g/5 g

WARNINGS

This product contains soy and its products, used with caution for allergies

INACTIVE INGREDIENT

Noni, Xiaoben Hongling Grass, Green South African Dr. Tea, Patented Fermented Daphnia Extract, Chrysanthemum Polyphenols, Guava, Sour Cherry

INDICATIONS AND USAGE

Add 150ml of water at room temperature every time, shake it and use it.

KEEP OUT OF REACH OF CHIL DREN SECTION

PURPOSE

Supplement the protein needed by the human body

ACTIVE INGREDIENT

Folic acid

DOSAGE AND ADMINISTRATION

Every time a bag, every day...